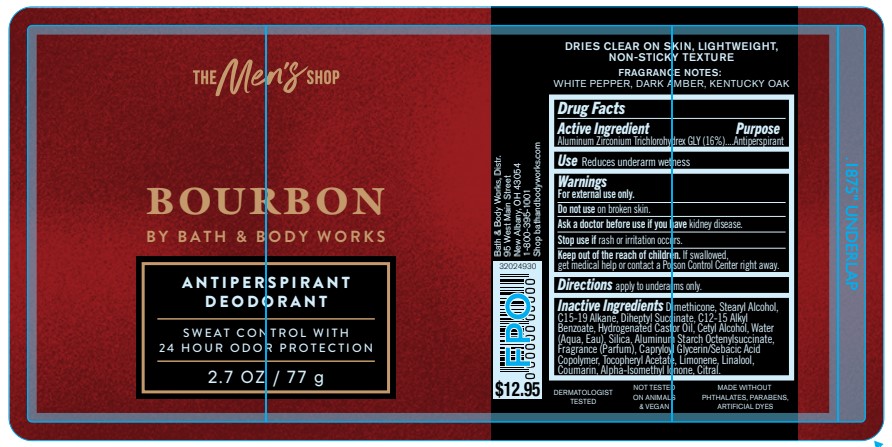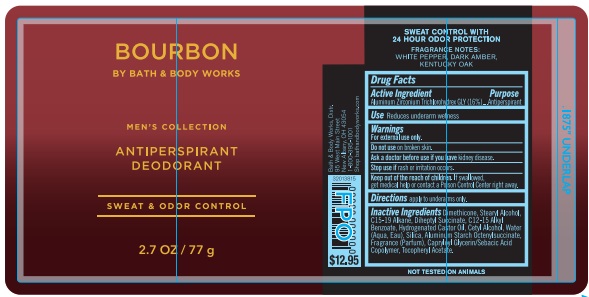 DRUG LABEL: Mens Collection Antiperspirant Deodorant
NDC: 62670-6707 | Form: STICK
Manufacturer: Bath and Body Works, Distr.
Category: otc | Type: HUMAN OTC DRUG LABEL
Date: 20260302

ACTIVE INGREDIENTS: ALUMINUM ZIRCONIUM TRICHLOROHYDREX GLY 16 g/100 g
INACTIVE INGREDIENTS: WATER

MC AP DEO Bourbon
(version2: updated artwork, added fragrance allergens)

Active Ingredient

Aluminum Zirconium Trichlorohydrex GLY 16%

PURPOSE

Antiperspirant

Use

Reduces underarm wetness

WARNINGS

For external use only.

Do not use on broken skin.

Ask a doctor before use if you have kidney disease.

Stop use if rash or irritation occurs.

Keep out of reach of children. If swallowed, get medical help or contact a Poison Control Center right away.

Directions

apply to underarms only.

Inactive Ingredients

Dimethicone, Stearyl Alcohol, C15-19 Alkane, Diheptyl Succinate, C12-15 Alkyl Benzoate, Hydrogenated Castor Oil, Cetyl Alcohol, Water (Aqua, Eau), Silica, Aluminum Starch Octenylsuccinate, Fragrance (Parfum), Capryloyl Glycerin/Sebacic Acid Copolymer, Tocopheryl Acetate, Limonene, Linalool, Coumarin, Alpha-Isomethyl Ionone, Citral

Bath & Body Works, Distr.

95 West Main Street

New Albany, OH 43054

1-800-395-1001

Shop bathandbodyworks.com